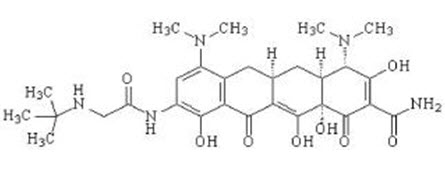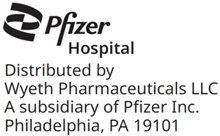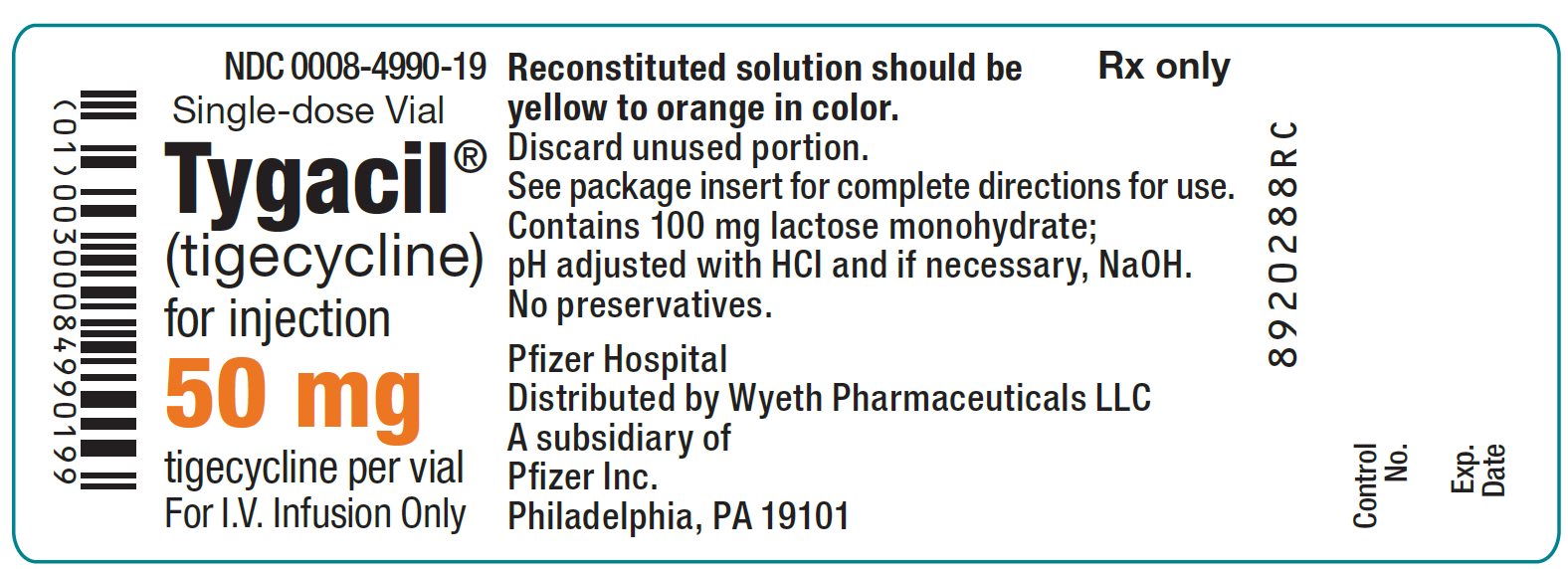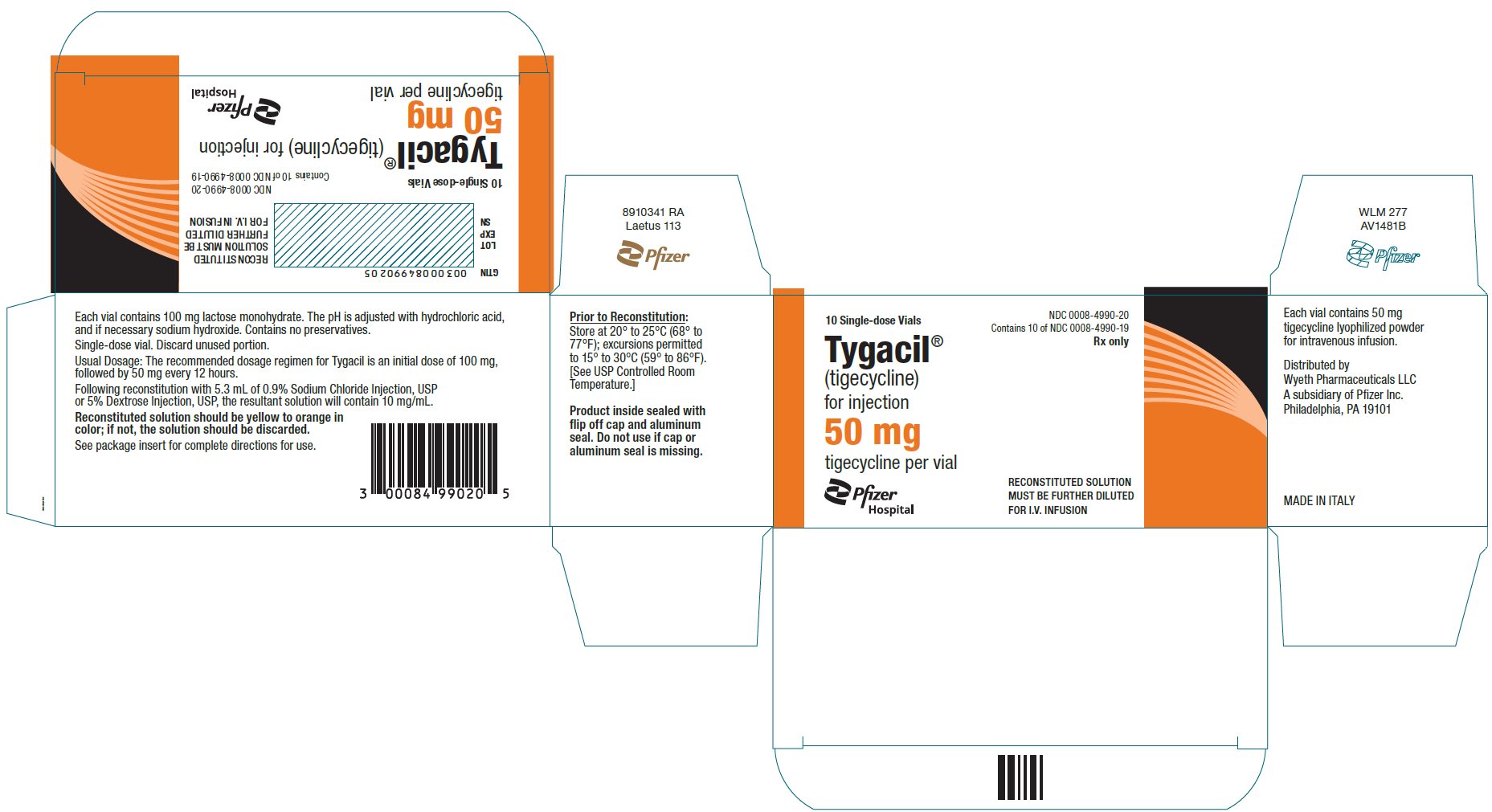 DRUG LABEL: Tygacil
NDC: 0008-4990 | Form: INJECTION, POWDER, LYOPHILIZED, FOR SOLUTION
Manufacturer: Wyeth Pharmaceuticals LLC, a subsidiary of Pfizer Inc.
Category: prescription | Type: HUMAN PRESCRIPTION DRUG LABEL
Date: 20251118

ACTIVE INGREDIENTS: TIGECYCLINE 50 mg/5 mL
INACTIVE INGREDIENTS: HYDROCHLORIC ACID; SODIUM HYDROXIDE; LACTOSE MONOHYDRATE 100 mg/5 mL

HIGHLIGHTS OF PRESCRIBING INFORMATION

These highlights do not include all the information needed to use TYGACIL safely and effectively. See full prescribing information for TYGACIL.
TYGACIL® (tigecycline) for injection, for intravenous use
Initial U.S. Approval: 2005

WARNING: ALL-CAUSE MORTALITY

See full prescribing information for complete boxed warning.

All-cause mortality was higher in patients treated with TYGACIL than comparators in a meta-analysis of clinical trials. The cause of this mortality risk difference of 0.6% (95% CI 0.1, 1.2) has not been established. TYGACIL should be reserved for use in situations when alternative treatments are not suitable (1.4, 5.1, 5.2, 6.1).

RECENT MAJOR CHANGES

Contraindications (4) | 3/2025
Warnings and precautions, Tetracycline-Class Adverse Effects (5.11) | 3/2025

1 INDICATIONS AND USAGE

TYGACIL is a tetracycline class antibacterial indicated in patients 18 years of age and older for:

- Complicated skin and skin structure infections (1.1)
- Complicated intra-abdominal infections (1.2)
- Community-acquired bacterial pneumonia (1.3)

Limitations of Use: TYGACIL is not indicated for treatment of diabetic foot infection or hospital-acquired pneumonia, including ventilator-associated pneumonia (1.4).

To reduce the development of drug-resistant bacteria and maintain the effectiveness of TYGACIL and other antibacterial drugs, TYGACIL should be used only to treat infections that are proven or strongly suspected to be caused by bacteria (1.5).

2 DOSAGE AND ADMINISTRATION

- Initial dose of 100 mg followed by 50 mg every 12 hours administered intravenously over approximately 30 to 60 minutes. (2.1)
- Severe hepatic impairment (Child Pugh C): Initial dose of 100 mg followed by 25 mg every 12 hours. (2.2)
- Obtain baseline blood coagulation parameters, including fibrinogen, and continue to monitor regularly during treatment with TYGACIL. (2.4, 5.6)

3 DOSAGE FORMS AND STRENGTHS

For Injection: 50 mg, lyophilized powder for reconstitution in a single-dose 10 mL vial. (3)

4 CONTRAINDICATIONS

- Known hypersensitivity to tigecycline. (4)

5 WARNINGS AND PRECAUTIONS

- All-Cause Mortality: A meta-analysis of Phase 3 and 4 clinical trials demonstrated an increase in all-cause mortality in TYGACIL-treated patients compared to controls with a risk difference of 0.6% (95% CI 0.1, 1.2). The cause of this increase has not been established. An increase was also seen in a meta-analysis limited to the approved indications [0.6% (95% CI 0.0, 1.2)]. The greatest difference in mortality was seen in TYGACIL-treated patients with ventilator-associated pneumonia. (5.1, 5.2)
- Anaphylactic Reactions: have been reported with TYGACIL, and may be life-threatening. Avoid use in patients with known hypersensitivity to tetracyclines. (5.3)
- Hepatic Adverse Effects: have been reported with TYGACIL. Patients who develop abnormal liver function tests during TYGACIL therapy should be monitored for evidence of worsening hepatic function and evaluated for risk/benefit of continuing tigecycline therapy. (5.4)
- Pancreatitis: including fatalities, has been reported with TYGACIL. If pancreatitis is suspected, then consider stopping TYGACIL. (5.5)
- Monitoring Blood Coagulation Parameters: Hypofibrinogenemia has been reported with TYGACIL. Monitor blood coagulation parameters, including fibrinogen, at baseline and regularly during treatment with TYGACIL. (5.6)
- Tooth Discoloration and Enamel Hypoplasia: The use of TYGACIL during tooth development (last half of pregnancy, infancy, and childhood to the age of 8 years) may cause permanent discoloration of the teeth (yellow-gray-brown) and enamel hypoplasia. (5.7)
- Inhibition of Bone Growth: The use of TYGACIL during the second and third trimester of pregnancy, infancy, and childhood up to the age of 8 years may cause reversible inhibition of bone growth. (5.8)
- Clostridioides difficile-Associated Diarrhea (CDAD): evaluate if diarrhea occurs. (5.9)

6 ADVERSE REACTIONS

The most common adverse reactions (incidence >5%) are nausea, vomiting, diarrhea, abdominal pain, headache, and increased SGPT. (6.1)

To report SUSPECTED ADVERSE REACTIONS, contact Pfizer Inc. at 1-800-438-1985 or FDA at 1-800-FDA-1088 or www.fda.gov/medwatch.

7 DRUG INTERACTIONS

- Warfarin: Suitable anticoagulation test should be monitored if TYGACIL is administered to patients receiving warfarin. (7.1)
- Calcineurin Inhibitors: Serum concentrations of calcineurin inhibitors (e.g., tacrolimus, cyclosporine) should be monitored during treatment with TYGACIL due to risk of toxicity. (7.2)

8 USE IN SPECIFIC POPULATIONS

- Lactation: Avoid breastfeeding for longer than 3 weeks while taking TYGACIL. A lactating woman may also pump and discard breast milk during treatment and for 9 days after the last dose of TYGACIL (8.2)
- Pediatrics: Use in patients under 18 years of age is not recommended. Pediatric trials were not conducted because of the higher risk of mortality seen in adult trials (8.4)

FULL PRESCRIBING INFORMATION

WARNING: ALL-CAUSE MORTALITY

An increase in all-cause mortality has been observed in a meta-analysis of Phase 3 and 4 clinical trials in TYGACIL-treated patients versus comparator. The cause of this mortality risk difference of 0.6% (95% CI 0.1, 1.2) has not been established. TYGACIL should be reserved for use in situations when alternative treatments are not suitable [see Indications and Usage (1.4), Warnings and Precautions (5.1, 5.2) and Adverse Reactions (6.1)].

1 INDICATIONS AND USAGE

1.1 Complicated Skin and Skin Structure Infections

TYGACIL is indicated in patients 18 years of age and older for the treatment of complicated skin and skin structure infections caused by susceptible isolates of Escherichia coli, Enterococcus faecalis (vancomycin-susceptible isolates), Staphylococcus aureus (methicillin-susceptible and -resistant isolates), Streptococcus agalactiae, Streptococcus anginosus grp. (includes S. anginosus, S. intermedius, and S. constellatus), Streptococcus pyogenes, Enterobacter cloacae, Klebsiella pneumoniae, and Bacteroides fragilis.

1.2 Complicated Intra-abdominal Infections

TYGACIL is indicated in patients 18 years of age and older for the treatment of complicated intra-abdominal infections caused by susceptible isolates of Citrobacter freundii, Enterobacter cloacae, Escherichia coli, Klebsiella oxytoca, Klebsiella pneumoniae, Enterococcus faecalis (vancomycin-susceptible isolates), Staphylococcus aureus (methicillin-susceptible and -resistant isolates), Streptococcus anginosus grp. (includes S. anginosus, S. intermedius, and S. constellatus), Bacteroides fragilis, Bacteroides thetaiotaomicron, Bacteroides uniformis, Bacteroides vulgatus, Clostridium perfringens, and Peptostreptococcus micros.

1.3 Community-Acquired Bacterial Pneumonia

TYGACIL is indicated in patients 18 years of age and older for the treatment of community-acquired bacterial pneumonia caused by susceptible isolates of Streptococcus pneumoniae (penicillin-susceptible isolates), including cases with concurrent bacteremia, Haemophilus influenzae, and Legionella pneumophila.

1.4 Limitations of Use

TYGACIL is not indicated for the treatment of diabetic foot infections. A clinical trial failed to demonstrate non-inferiority of TYGACIL for treatment of diabetic foot infections.

TYGACIL is not indicated for the treatment of hospital-acquired or ventilator-associated pneumonia. In a comparative clinical trial, greater mortality and decreased efficacy were reported in TYGACIL-treated patients [see Warnings and Precautions (5.2)].

1.5 Usage

To reduce the development of drug-resistant bacteria and maintain the effectiveness of TYGACIL and other antibacterial drugs, TYGACIL should be used only to treat infections that are proven or strongly suspected to be caused by susceptible bacteria. When culture and susceptibility information are available, they should be considered in selecting or modifying antibacterial therapy. In the absence of such data, local epidemiology and susceptibility patterns may contribute to the empiric selection of therapy.

Appropriate specimens for bacteriological examination should be obtained in order to isolate and identify the causative organisms and to determine their susceptibility to tigecycline. TYGACIL may be initiated as empiric monotherapy before results of these tests are known.

2 DOSAGE AND ADMINISTRATION

2.1 Recommended Adult Dosage

The recommended dosage regimen for TYGACIL is an initial dose of 100 mg, followed by 50 mg every 12 hours. Intravenous infusions of TYGACIL should be administered over approximately 30 to 60 minutes every 12 hours.

The recommended duration of treatment with TYGACIL for complicated skin and skin structure infections or for complicated intra-abdominal infections is 5 to 14 days. The recommended duration of treatment with TYGACIL for community-acquired bacterial pneumonia is 7 to 14 days. The duration of therapy should be guided by the severity and site of the infection and the patient's clinical and bacteriological progress.

2.2 Dosage in Patients With Hepatic Impairment

No dosage adjustment is warranted in patients with mild to moderate hepatic impairment (Child Pugh A and Child Pugh B). In patients with severe hepatic impairment (Child Pugh C), the initial dose of TYGACIL should be 100 mg followed by a reduced maintenance dose of 25 mg every 12 hours. Patients with severe hepatic impairment (Child Pugh C) should be treated with caution and monitored for treatment response [see Clinical Pharmacology (12.3) and Use in Specific Populations (8.6)].

2.3 Dosage in Pediatric Patients

The safety and efficacy of the proposed pediatric dosing regimens have not been evaluated due to the observed increase in mortality associated with TYGACIL in adult patients. Avoid use of TYGACIL in pediatric patients unless no alternative antibacterial drugs are available. Under these circumstances, the following doses are suggested:

- Pediatric patients aged 8 to 11 years should receive 1.2 mg/kg of TYGACIL every 12 hours intravenously to a maximum dose of 50 mg of TYGACIL every 12 hours.
- Pediatric patients aged 12 to 17 years should receive 50 mg of TYGACIL every 12 hours.

The proposed pediatric doses of TYGACIL were chosen based on exposures observed in pharmacokinetic trials, which included small numbers of pediatric patients [see Use in Specific Populations (8.4) and Clinical Pharmacology (12.3)].

There are no data to provide dosing recommendations in pediatric patients with hepatic impairment.

2.4 Monitoring of Blood Coagulation Parameters

Obtain baseline blood coagulation parameters, including fibrinogen, and continue to monitor regularly during treatment with TYGACIL [see Warnings and Precautions (5.6)].

2.5 Preparation and Administration

Each vial of TYGACIL should be reconstituted with 5.3 mL of 0.9% Sodium Chloride Injection, USP, 5% Dextrose Injection, USP, or Lactated Ringer's Injection, USP to achieve a concentration of 10 mg/mL of tigecycline. (Note: Each vial contains a 6% overage. Thus, 5 mL of reconstituted solution is equivalent to 50 mg of the drug.) The vial should be gently swirled until the drug dissolves. Reconstituted solution must be transferred and further diluted for intravenous infusion. Withdraw 5 mL of the reconstituted solution from the vial and add to a 100 mL intravenous bag for infusion (for a 100 mg dose, reconstitute two vials; for a 50 mg dose, reconstitute one vial). The maximum concentration in the intravenous bag should be 1 mg/mL. The reconstituted solution should be yellow to orange in color; if not, the solution should be discarded. Parenteral drug products should be inspected visually for particulate matter and discoloration (e.g., green or black) prior to administration. Once reconstituted, TYGACIL may be stored at room temperature (not to exceed 25°C/77°F) for up to 24 hours (up to 6 hours in the vial and the remaining time in the intravenous bag). If the storage conditions exceed 25°C (77°F) after reconstitution, tigecycline should be used immediately. Alternatively, TYGACIL mixed with 0.9% Sodium Chloride Injection, USP or 5% Dextrose Injection, USP may be stored refrigerated at 2° to 8°C (36° to 46°F) for up to 48 hours following immediate transfer of the reconstituted solution into the intravenous bag.

TYGACIL may be administered intravenously through a dedicated line or through a Y-site. If the same intravenous line is used for sequential infusion of several drugs, the line should be flushed before and after infusion of TYGACIL with 0.9% Sodium Chloride Injection, USP, 5% Dextrose Injection, USP or Lactated Ringer's Injection, USP. Injection should be made with an infusion solution compatible with tigecycline and with any other drug(s) administered via this common line.

2.6 Drug Compatibilities

Compatible intravenous solutions include 0.9% Sodium Chloride Injection, USP, 5% Dextrose Injection, USP, and Lactated Ringer's Injection, USP. When administered through a Y-site, TYGACIL is compatible with the following drugs or diluents when used with either 0.9% Sodium Chloride Injection, USP or 5% Dextrose Injection, USP: amikacin, dobutamine, dopamine HCl, gentamicin, haloperidol, Lactated Ringer's, lidocaine HCl, metoclopramide, morphine, norepinephrine, piperacillin/tazobactam (EDTA formulation), potassium chloride, propofol, ranitidine HCl, theophylline, and tobramycin.

2.7 Drug Incompatibilities

The following drugs should not be administered simultaneously through the same Y-site as TYGACIL: amphotericin B, amphotericin B lipid complex, diazepam, esomeprazole, and omeprazole.

3 DOSAGE FORMS AND STRENGTHS

For Injection: Each single-dose 10 mL glass vial contain 50 mg of tigecycline as an orange lyophilized powder for reconstitution.

4 CONTRAINDICATIONS

TYGACIL is contraindicated for use in patients who have known hypersensitivity to tigecycline or to any of the excipients. Reactions have included anaphylactic reactions [see Warnings and Precautions (5.3) and Adverse Reactions (6.2)].

5 WARNINGS AND PRECAUTIONS

5.1 All-Cause Mortality

An increase in all-cause mortality has been observed in a meta-analysis of Phase 3 and 4 clinical trials in TYGACIL-treated patients versus comparator-treated patients. In all 13 Phase 3 and 4 trials that included a comparator, death occurred in 4.0% (150/3788) of patients receiving TYGACIL and 3.0% (110/3646) of patients receiving comparator drugs. In a pooled analysis of these trials, based on a random effects model by trial weight, the adjusted risk difference of all-cause mortality was 0.6% (95% CI 0.1, 1.2) between TYGACIL and comparator-treated patients. An analysis of mortality in all trials conducted for approved indications (cSSSI, cIAI, and CABP), including post-market trials showed an adjusted mortality rate of 2.5% (66/2640) for tigecycline and 1.8% (48/2628) for comparator, respectively. The adjusted risk difference for mortality stratified by trial weight was 0.6% (95% CI 0.0, 1.2).

The cause of this mortality difference has not been established. Generally, deaths were the result of worsening infection, complications of infection or underlying co-morbidities. TYGACIL should be reserved for use in situations when alternative treatments are not suitable [see Boxed Warning, Indications and Usage (1.4), Warnings and Precautions (5.2) and Adverse Reactions (6.1)].

5.2 Mortality Imbalance and Lower Cure Rates in Hospital-Acquired Pneumonia

A trial of patients with hospital acquired, including ventilator-associated, pneumonia failed to demonstrate the efficacy of TYGACIL. In this trial, patients were randomized to receive TYGACIL (100 mg initially, then 50 mg every 12 hours) or a comparator. In addition, patients were allowed to receive specified adjunctive therapies. The sub-group of patients with ventilator-associated pneumonia who received TYGACIL had lower cure rates (47.9% versus 70.1% for the clinically evaluable population).

In this trial, greater mortality was seen in patients with ventilator-associated pneumonia who received TYGACIL (25/131 [19.1%] versus 15/122 [12.3%] in comparator-treated patients) [see Adverse Reactions (6.1)]. Particularly high mortality was seen among TYGACIL-treated patients with ventilator-associated pneumonia and bacteremia at baseline (9/18 [50.0%] versus 1/13 [7.7%] in comparator-treated patients).

5.3 Anaphylactic Reactions

Anaphylactic reactions have been reported with nearly all antibacterial agents, including TYGACIL, and may be life-threatening. TYGACIL is structurally similar to tetracycline-class antibacterial drugs and should be avoided in patients with known hypersensitivity to tetracycline-class antibacterial drugs.

5.4 Hepatic Adverse Effects

Increases in total bilirubin concentration, prothrombin time and transaminases have been seen in patients treated with tigecycline. Isolated cases of significant hepatic dysfunction and hepatic failure have been reported in patients being treated with tigecycline. Some of these patients were receiving multiple concomitant medications. Patients who develop abnormal liver function tests during tigecycline therapy should be monitored for evidence of worsening hepatic function and evaluated for risk/benefit of continuing tigecycline therapy. Hepatic dysfunction may occur after the drug has been discontinued.

5.5 Pancreatitis

Acute pancreatitis, including fatal cases, has occurred in association with tigecycline treatment. The diagnosis of acute pancreatitis should be considered in patients taking tigecycline who develop clinical symptoms, signs, or laboratory abnormalities suggestive of acute pancreatitis. Cases have been reported in patients without known risk factors for pancreatitis. Patients usually improve after tigecycline discontinuation. Consideration should be given to the cessation of the treatment with tigecycline in cases suspected of having developed pancreatitis [see Adverse Reactions (6.2)].

5.6 Monitoring of Blood Coagulation Parameters

Hypofibrinogenemia has been reported in patients treated with TYGACIL [see Adverse Reactions (6.2)]. Obtain baseline blood coagulation parameters, including fibrinogen, and continue to monitor regularly during treatment with TYGACIL.

5.7 Tooth Discoloration and Enamel Hypoplasia

The use of TYGACIL during tooth development (last half of pregnancy, infancy, and childhood to the age of 8 years) may cause permanent discoloration of the teeth (yellow-gray-brown). This adverse reaction is more common during long-term use of tetracyclines, but it has been observed following repeated short-term courses. Enamel hypoplasia has also been reported. Advise the patient of the potential risk to the fetus if TYGACIL is used during the second or third trimester of pregnancy [see Use in Specific Populations (8.1, 8.4)].

5.8 Inhibition of Bone Growth

The use of TYGACIL during the second and third trimester of pregnancy, infancy and childhood up to the age of 8 years may cause reversible inhibition of bone growth. All tetracyclines form a stable calcium complex in any bone-forming tissue. A decrease in fibula growth rate has been observed in premature infants given oral tetracycline in doses of 25 mg/kg every 6 hours. This reaction was shown to be reversible when the tetracycline was discontinued. Advise the patient of the potential risk to the fetus if TYGACIL is used during the second or third trimester of pregnancy [see Use in Specific Populations (8.1, 8.4)].

5.9 Clostridioides difficile-Associated Diarrhea

Clostridioides difficile-associated diarrhea (CDAD) has been reported with use of nearly all antibacterial agents, including TYGACIL, and may range in severity from mild diarrhea to fatal colitis. Treatment with antibacterial agents alters the normal flora of the colon leading to overgrowth of C. difficile.

C. difficile produces toxins A and B which contribute to the development of CDAD. Hypertoxin producing strains of C. difficile cause increased morbidity and mortality, as these infections can be refractory to antimicrobial therapy and may require colectomy. CDAD must be considered in all patients who present with diarrhea following antibacterial drug use. Careful medical history is necessary since CDAD has been reported to occur over two months after the administration of antibacterial agents.

If CDAD is suspected or confirmed, ongoing antibacterial drug use not directed against C. difficile may need to be discontinued. Appropriate fluid and electrolyte management, protein supplementation, antibacterial drug treatment of C. difficile, and surgical evaluation should be instituted as clinically indicated.

5.10 Sepsis/Septic Shock in Patients With Intestinal Perforation

Monotherapy with tigecycline should be avoided in patients with complicated intra-abdominal infections (cIAI) secondary to clinically apparent intestinal perforation. In cIAI studies (n=1642), 6 patients treated with TYGACIL and 2 patients treated with imipenem/cilastatin presented with intestinal perforations and developed sepsis/septic shock. The 6 patients treated with TYGACIL had higher APACHE II scores (median = 13) versus the 2 patients treated with imipenem/cilastatin (APACHE II scores = 4 and 6). Due to differences in baseline APACHE II scores between treatment groups and small overall numbers, the relationship of this outcome to treatment cannot be established.

5.11 Tetracycline-Class Adverse Effects

TYGACIL is structurally similar to tetracycline-class antibacterial drugs and may have similar adverse effects. Such effects may include: photosensitivity, fixed drug eruption, pseudotumor cerebri, and anti-anabolic action (which has led to increased BUN, azotemia, acidosis, and hyperphosphatemia). Discontinue TYGACIL if any of these adverse reactions are suspected.

5.12 Development of Drug-Resistant Bacteria

Prescribing TYGACIL in the absence of a proven or strongly suspected bacterial infection is unlikely to provide benefit to the patient and increases the risk of the development of drug-resistant bacteria.

6 ADVERSE REACTIONS

The following serious adverse reactions are described elsewhere in the labeling:

- All-Cause Mortality [see Boxed Warning and Warnings and Precautions (5.1)]
- Mortality Imbalance and Lower Cure Rates in Hospital-Acquired Pneumonia [see Warnings and Precautions (5.2)]
- Anaphylaxis [Warning and Precautions (5.3)]
- Hepatic Adverse Effects [Warnings and Precautions (5.4)]
- Pancreatitis [Warnings and Precautions (5.5)]

6.1 Clinical Trials Experience

Because clinical trials are conducted under widely varying conditions, adverse reaction rates observed in the clinical trials of a drug cannot be directly compared to rates in the clinical trials of another drug and may not reflect the rates observed in practice.

In clinical trials, 2514 patients were treated with TYGACIL. TYGACIL was discontinued due to adverse reactions in 7% of patients compared to 6% for all comparators. Table 1 shows the incidence of adverse reactions through test of cure reported in ≥2% of patients in these trials.

Table 1. Incidence (%) of Adverse Reactions Through Test of Cure Reported in ≥ 2% of Patients Treated in Clinical Studies
Body System Adverse Reactions | TYGACIL (N=2514) | Comparators [Vancomycin/Aztreonam, Imipenem/Cilastatin, Levofloxacin, Linezolid.] (N=2307)
Body as a Whole
Abdominal pain | 6 | 4
Abscess | 2 | 2
Asthenia | 3 | 2
Headache | 6 | 7
Infection | 7 | 5
Cardiovascular System
Phlebitis | 3 | 4
Digestive System
Diarrhea | 12 | 11
Dyspepsia | 2 | 2
Nausea | 26 | 13
Vomiting | 18 | 9
Hemic and Lymphatic System
Anemia | 5 | 6
Metabolic and Nutritional
Alkaline Phosphatase Increased | 3 | 3
Amylase Increased | 3 | 2
Bilirubinemia | 2 | 1
BUN Increased | 3 | 1
Healing Abnormal | 3 | 2
Hyponatremia | 2 | 1
Hypoproteinemia | 5 | 3
SGOT Increased [LFT abnormalities in TYGACIL-treated patients were reported more frequently in the post therapy period than those in comparator-treated patients, which occurred more often on therapy.] | 4 | 5
SGPT Increased | 5 | 5
Respiratory System
Pneumonia | 2 | 2
Nervous System
Dizziness | 3 | 3
Skin and Appendages
Rash | 3 | 4

In all 13 Phase 3 and 4 trials that included a comparator, death occurred in 4.0% (150/3788) of patients receiving TYGACIL and 3.0% (110/3646) of patients receiving comparator drugs. In a pooled analysis of these trials, based on a random effects model by trial weight, an adjusted risk difference of all-cause mortality was 0.6% (95% CI 0.1, 1.2) between TYGACIL and comparator-treated patients (see Table 2). The cause of the imbalance has not been established. Generally, deaths were the result of worsening infection, complications of infection or underlying co-morbidities.

Table 2. Patients with Outcome of Death by Infection Type
 | TYGACIL |  | Comparator |  | Risk Difference [The difference between the percentage of patients who died in TYGACIL and comparator treatment groups. The 95% CI for each infection type was calculated using the normal approximation method without continuity correction.]
Infection Type | n/N | % | n/N | % | % (95% CI)
cSSSI | 12/834 | 1.4 | 6/813 | 0.7 | 0.7 (-0.3, 1.7)
cIAI | 42/1382 | 3.0 | 31/1393 | 2.2 | 0.8 (-0.4, 2.0)
CAP | 12/424 | 2.8 | 11/422 | 2.6 | 0.2 (-2.0, 2.4)
HAP | 66/467 | 14.1 | 57/467 | 12.2 | 1.9 (-2.4, 6.3)
Non-VAP [These are subgroups of the HAP population.] | 41/336 | 12.2 | 42/345 | 12.2 | 0.0 (-4.9, 4.9)
VAP | 25/131 | 19.1 | 15/122 | 12.3 | 6.8 (-2.1, 15.7)
RP | 11/128 | 8.6 | 2/43 | 4.7 | 3.9 (-4.0, 11.9)
DFI | 7/553 | 1.3 | 3/508 | 0.6 | 0.7 (-0.5, 1.8)
Overall Adjusted | 150/3788 | 4.0 | 110/3646 | 3.0 | 0.6 (0.1, 1.2) [Overall adjusted (random effects model by trial weight) risk difference estimate and 95% CI.]
CAP = Community-acquired pneumonia; cIAI = Complicated intra-abdominal infections; cSSSI = Complicated skin and skin structure infections; HAP = Hospital-acquired pneumonia; VAP = Ventilator-associated pneumonia; RP = Resistant pathogens; DFI = Diabetic foot infections.
Note: The studies include 300, 305, 900 (cSSSI), 301, 306, 315, 316, 400 (cIAI), 308 and 313 (CAP), 311 (HAP), 307 [Resistant gram-positive pathogen study in patients with MRSA or Vancomycin-Resistant Enterococcus (VRE)], and 319 (DFI with and without osteomyelitis).

An analysis of mortality in all trials conducted for approved indications - cSSSI, cIAI, and CABP, including post-market trials (one in cSSSI and two in cIAI) - showed an adjusted mortality rate of 2.5% (66/2640) for tigecycline and 1.8% (48/2628) for comparator, respectively. The adjusted risk difference for mortality stratified by trial weight was 0.6% (95% CI 0.0, 1.2).

In comparative clinical studies, infection-related serious adverse reactions were more frequently reported for subjects treated with TYGACIL (7%) versus comparators (6%). Serious adverse reactions of sepsis/septic shock were more frequently reported for subjects treated with TYGACIL (2%) versus comparators (1%). Due to baseline differences between treatment groups in this subset of patients, the relationship of this outcome to treatment cannot be established [see Warnings and Precautions (5.10)].

The most common adverse reactions were nausea and vomiting which generally occurred during the first 1 – 2 days of therapy. The majority of cases of nausea and vomiting associated with TYGACIL and comparators were either mild or moderate in severity. In patients treated with TYGACIL, nausea incidence was 26% (17% mild, 8% moderate, 1% severe) and vomiting incidence was 18% (11% mild, 6% moderate, 1% severe).

In patients treated for complicated skin and skin structure infections (cSSSI), nausea incidence was 35% for TYGACIL and 9% for vancomycin/aztreonam; vomiting incidence was 20% for TYGACIL and 4% for vancomycin/aztreonam. In patients treated for complicated intra-abdominal infections (cIAI), nausea incidence was 25% for TYGACIL and 21% for imipenem/cilastatin; vomiting incidence was 20% for TYGACIL and 15% for imipenem/cilastatin. In patients treated for community-acquired bacterial pneumonia (CABP), nausea incidence was 24% for TYGACIL and 8% for levofloxacin; vomiting incidence was 16% for TYGACIL and 6% for levofloxacin.

Discontinuation from TYGACIL was most frequently associated with nausea (1%) and vomiting (1%). For comparators, discontinuation was most frequently associated with nausea (<1%).

The following adverse reactions were reported (<2%) in patients receiving TYGACIL in clinical studies:

Body as a Whole: injection site inflammation, injection site pain, injection site reaction, septic shock, allergic reaction, chills, injection site edema, injection site phlebitis

Cardiovascular System: thrombophlebitis

Digestive System: anorexia, jaundice, abnormal stools

Metabolic/Nutritional System: increased creatinine, hypocalcemia, hypoglycemia

Special Senses: taste perversion

Hemic and Lymphatic System: prolonged activated partial thromboplastin time (aPTT), prolonged prothrombin time (PT), eosinophilia, increased international normalized ratio (INR), thrombocytopenia

Skin and Appendages: pruritus

Urogenital System: vaginal moniliasis, vaginitis, leukorrhea

6.2 Postmarketing Experience

The following adverse reactions have been identified during post-approval use of TYGACIL. Because these reactions are reported voluntarily from a population of uncertain size, it is not always possible to reliably estimate their frequency or establish causal relationship to drug exposure.

- anaphylactic reactions
- acute pancreatitis
- hepatic cholestasis, and jaundice
- severe skin reactions, including Stevens-Johnson Syndrome
- symptomatic hypoglycemia in patients with and without diabetes mellitus
- hypofibrinogenemia [see Warnings and Precautions (5.6)]

7 DRUG INTERACTIONS

7.1 Warfarin

Prothrombin time or other suitable anticoagulation test should be monitored if TYGACIL is administered with warfarin [see Clinical Pharmacology (12.3)].

7.2 Calcineurin Inhibitors

Concomitant use of TYGACIL and calcineurin inhibitors such as tacrolimus or cyclosporine may lead to an increase in serum trough concentrations of the calcineurin inhibitors. Therefore, serum concentrations of the calcineurin inhibitor should be monitored during treatment with TYGACIL to avoid drug toxicity.

7.3 Oral Contraceptives

Concurrent use of antibacterial drugs with oral contraceptives may render oral contraceptives less effective.

8 USE IN SPECIFIC POPULATIONS

8.1 Pregnancy

Risk Summary

TYGACIL, like other tetracycline class antibacterial drugs, may cause permanent discoloration of deciduous teeth and reversible inhibition of bone growth when administered during the second and third trimesters of pregnancy [see Warnings and Precautions (5.7, 5.8), Data, and Use in Specific Populations (8.4)]. There are no available data on the risk of major birth defects or miscarriage following the use of TYGACIL during pregnancy. Administration of intravenous tigecycline in pregnant rats and rabbits during the period of organogenesis was associated with reduction in fetal weights and an increased incidence of skeletal anomalies (delays in bone ossification) at exposures of 5 and 1 times the human exposure at the recommended clinical dose in rats and rabbits, respectively. Advise the patient of the potential risk to the fetus if TYGACIL is used during the second or third trimester.

The estimated background risk of major birth defects and miscarriage for the indicated population is unknown. All pregnancies have a background risk of birth defect, loss, or other adverse outcomes. In the U. S. general population, the estimated background risk in clinically recognized pregnancies is 2 to 4% and 15 to 20%, respectively.

Data

Human Data

The use of tetracycline-class antibacterial drugs, that includes TYGACIL, during tooth development (second and third trimester of pregnancy) may cause permanent discoloration of deciduous teeth. This adverse reaction is more common during long-term use of tetracyclines but has been observed following repeated short-term courses. TYGACIL may cause reversible inhibition of bone growth when administered during the second and third trimesters of pregnancy. A decrease in fibula growth rate has been observed in premature infants given oral tetracycline in doses of 25 mg/kg every 6 hours.

Animal Data

In embryo-fetal development studies, tigecycline was administered during the period of organogenesis at doses up to 12 mg/kg/day in rats and 4 mg/kg in rabbits or 5 and 1 times the systemic exposure at the recommended clinical dose, respectively. In the rat study, decreased fetal weight and fetal skeletal variations (reduced ossification of the pubic, ischial, and supraoccipital bones and increased incidences of rudimentary 14th rib) were observed in the presence of maternal toxicity at 12 mg/kg/day (5 times the recommended clinical dose based on systemic exposure). In rabbits, decreased fetal weights were observed in the presence of maternal toxicity at 4 mg/kg (equivalent to the human exposure at the recommended clinical dose).

In preclinical safety studies, ^14C-labeled tigecycline crossed the placenta and was found in fetal tissues.

8.2 Lactation

Risk Summary

There are no data on the presence of tigecycline in human milk; however, tetracycline-class antibacterial drugs are present in breast milk. It is not known whether tigecycline has an effect on the breastfed infant or on milk production. Tigecycline has low oral bioavailability; therefore, infant exposure is expected to be low. Tigecycline is present in rat milk with little or no systemic exposure to tigecycline in nursing pups as a result of exposure via maternal milk. When a drug is present in animal milk, it is likely that the drug will be present in human milk.

The developmental and health benefits of breastfeeding should be considered along with the mother's clinical need for TYGACIL and any potential adverse effects on the breastfed child from TYGACIL or from the underlying maternal condition (see Clinical Considerations).

Clinical Considerations

Because of the theoretical risk of dental discoloration and inhibition of bone growth, avoid breastfeeding if taking TYGACIL for longer than three weeks. A lactating woman may also consider interrupting breastfeeding and pumping and discarding breastmilk during administration of TYGACIL and for 9 days (approximately 5 half-lives) after the last dose in order to minimize drug exposure to a breastfed infant.

8.4 Pediatric Use

Use in patients under 18 years of age is not recommended. Safety and effectiveness in pediatric patients below the age of 18 years have not been established. Because of the increased mortality observed in TYGACIL-treated adult patients in clinical trials, pediatric trials of TYGACIL to evaluate the safety and efficacy of TYGACIL were not conducted.

In situations where there are no other alternative antibacterial drugs, dosing has been proposed for pediatric patients 8 to 17 years of age based on data from pediatric pharmacokinetic studies [see Dosage and Administration (2.3) and Clinical Pharmacology (12.3)].

Because of effects on tooth development, use in patients under 8 years of age is not recommended [see Warnings and Precautions (5.7)].

8.5 Geriatric Use

Of the total number of subjects who received TYGACIL in Phase 3 clinical studies (n=2514), 664 were 65 and over, while 288 were 75 and over. No overall differences in safety or effectiveness were observed between these subjects and younger subjects, but greater sensitivity to adverse events of some older individuals cannot be ruled out.

No significant difference in tigecycline exposure was observed between healthy elderly subjects and younger subjects following a single 100 mg dose of tigecycline [see Clinical Pharmacology (12.3)].

8.6 Hepatic Impairment

No dosage adjustment is warranted in patients with mild to moderate hepatic impairment (Child Pugh A and Child Pugh B). In patients with severe hepatic impairment (Child Pugh C), the initial dose of tigecycline should be 100 mg followed by a reduced maintenance dose of 25 mg every 12 hours. Patients with severe hepatic impairment (Child Pugh C) should be treated with caution and monitored for treatment response [see Clinical Pharmacology (12.3) and Dosage and Administration (2.2)].

10 OVERDOSAGE

No specific information is available on the treatment of overdosage with tigecycline. Intravenous administration of TYGACIL at a single dose of 300 mg over 60 minutes in healthy volunteers resulted in an increased incidence of nausea and vomiting. Tigecycline is not removed in significant quantities by hemodialysis.

11 DESCRIPTION

TYGACIL (tigecycline) is a tetracycline class antibacterial for intravenous infusion. The chemical name of tigecycline is (4S,4aS,5aR,12aS)-9-[2-(tert-butylamino)acetamido]-4,7-bis(dimethylamino)-1,4,4a,5,5a,6,11,12a-octahydro-3,10,12,12a-tetrahydroxy-1,11-dioxo-2-naphthacenecarboxamide. The empirical formula is C29H39N5O8 and the molecular weight is 585.65.

The following represents the chemical structure of tigecycline:

Figure 1: Structure of Tigecycline

TYGACIL is an orange lyophilized powder or cake. Each TYGACIL single-dose 10 mL vial contains 50 mg tigecycline lyophilized powder for reconstitution for intravenous infusion and 100 mg of lactose monohydrate. The pH is adjusted with hydrochloric acid, and if necessary sodium hydroxide. The product does not contain preservatives.

12 CLINICAL PHARMACOLOGY

12.1 Mechanism of Action

Tigecycline is a tetracycline class antibacterial [see Microbiology (12.4)].

12.2 Pharmacodynamics

Cardiac Electrophysiology

No significant effect of a single intravenous dose of TYGACIL 50 mg or 200 mg on QTc interval was detected in a randomized, placebo- and active-controlled four-arm crossover thorough QTc study of 46 healthy subjects.

12.3 Pharmacokinetics

The mean pharmacokinetic parameters of tigecycline after single and multiple intravenous doses based on pooled data from clinical pharmacology studies are summarized in Table 3. Intravenous infusions of tigecycline were administered over approximately 30 to 60 minutes.

Table 3. Mean (CV%) Pharmacokinetic Parameters of Tigecycline
 | Single Dose 100 mg (N=224) | Multiple Dose [100 mg initially, followed by 50 mg every 12 hours] 50 mg every 12h (N=103)
Cmax (mcg/mL) [30-minute infusion] | 1.45 (22%) | 0.87 (27%)
Cmax (mcg/mL) [60-minute infusion] | 0.90 (30%) | 0.63 (15%)
AUC (mcg∙h/mL) | 5.19 (36%) | - -
AUC0–24h (mcg∙h/mL) | - - | 4.70 (36%)
Cmin (mcg/mL) | - - | 0.13 (59%)
t½ (h) | 27.1 (53%) | 42.4 (83%)
CL (L/h) | 21.8 (40%) | 23.8 (33%)
CLr (mL/min) | 38.0 (82%) | 51.0 (58%)
Vss (L) | 568 (43%) | 639 (48%)

Distribution

The in vitro plasma protein binding of tigecycline ranges from approximately 71% to 89% at concentrations observed in clinical studies (0.1 to 1.0 mcg/mL). The steady-state volume of distribution of tigecycline averaged 500 to 700 L (7 to 9 L/kg), indicating tigecycline is extensively distributed beyond the plasma volume and into the tissues.

Following the administration of tigecycline 100 mg followed by 50 mg every 12 hours to 33 healthy volunteers, the tigecycline AUC0–12h (134 mcg∙h/mL) in alveolar cells was approximately 78-fold higher than the AUC0–12h in the serum, and the AUC0–12h (2.28 mcg∙h/mL) in epithelial lining fluid was approximately 32% higher than the AUC0–12h in serum. The AUC0–12h (1.61 mcg∙h/mL) of tigecycline in skin blister fluid was approximately 26% lower than the AUC0–12h in the serum of 10 healthy subjects.

In a single-dose study, tigecycline 100 mg was administered to subjects prior to undergoing elective surgery or medical procedure for tissue extraction. Concentrations at 4 hours after tigecycline administration were higher in gallbladder (38-fold, n=6), lung (3.7-fold, n=5), and colon (2.3-fold, n=6), and lower in synovial fluid (0.58-fold, n=5), and bone (0.35-fold, n=6) relative to serum. The concentration of tigecycline in these tissues after multiple doses has not been studied.

Elimination

Metabolism

Tigecycline is not extensively metabolized. In vitro studies with tigecycline using human liver microsomes, liver slices, and hepatocytes led to the formation of only trace amounts of metabolites. In healthy male volunteers receiving ^14C-tigecycline, tigecycline was the primary ^14C-labeled material recovered in urine and feces, but a glucuronide, an N-acetyl metabolite, and a tigecycline epimer (each at no more than 10% of the administered dose) were also present.

Tigecycline is a substrate of P-glycoprotein (P-gp) based on an in vitro study using a cell line overexpressing P-gp. The potential contribution of P-gp-mediated transport to the in vivo disposition of tigecycline is not known.

Excretion

The recovery of total radioactivity in feces and urine following administration of ^14C-tigecycline indicates that 59% of the dose is eliminated by biliary/fecal excretion, and 33% is excreted in urine. Approximately 22% of the total dose is excreted as unchanged tigecycline in urine. Overall, the primary route of elimination for tigecycline is biliary excretion of unchanged tigecycline and its metabolites. Glucuronidation and renal excretion of unchanged tigecycline are secondary routes.

Specific Populations

Hepatic Impairment

In a study comparing 10 patients with mild hepatic impairment (Child Pugh A), 10 patients with moderate hepatic impairment (Child Pugh B), and 5 patients with severe hepatic impairment (Child Pugh C) to 23 age and weight matched healthy control subjects, the single-dose pharmacokinetic disposition of tigecycline was not altered in patients with mild hepatic impairment. However, systemic clearance of tigecycline was reduced by 25% and the half-life of tigecycline was prolonged by 23% in patients with moderate hepatic impairment (Child Pugh B). Systemic clearance of tigecycline was reduced by 55%, and the half-life of tigecycline was prolonged by 43% in patients with severe hepatic impairment (Child Pugh C). Dosage adjustment is necessary in patients with severe hepatic impairment (Child Pugh C) [see Use in Specific Populations (8.6) and Dosage and Administration (2.2)].

Renal Impairment

A single dose study compared 6 subjects with severe renal impairment (creatinine clearance <30 mL/min), 4 end stage renal disease (ESRD) patients receiving tigecycline 2 hours before hemodialysis, 4 ESRD patients receiving tigecycline 1 hour after hemodialysis, and 6 healthy control subjects. The pharmacokinetic profile of tigecycline was not significantly altered in any of the renally impaired patient groups, nor was tigecycline removed by hemodialysis. No dosage adjustment of TYGACIL is necessary in patients with renal impairment or in patients undergoing hemodialysis.

Geriatric Patients

No significant differences in pharmacokinetics were observed between healthy elderly subjects (n=15, age 65–75; n=13, age >75) and younger subjects (n=18) receiving a single 100-mg dose of TYGACIL. Therefore, no dosage adjustment is necessary based on age [see Use in Specific Populations (8.5)].

Pediatric Patients

A single-dose safety, tolerability, and pharmacokinetic study of tigecycline in pediatric patients aged 8–16 years who recently recovered from infections was conducted. The doses administered were 0.5, 1, or 2 mg/kg. The study showed that for children aged 12–16 years (n = 16) a dosage of 50 mg twice daily would likely result in exposures comparable to those observed in adults with the approved dosing regimen. Large variability observed in children aged 8 to 11 years of age (n = 8) required additional study to determine the appropriate dosage.

A subsequent tigecycline dose-finding study was conducted in 8–11 year old patients with cIAI, cSSSI, or CABP. The doses of tigecycline studied were 0.75 mg/kg (n = 17), 1 mg/kg (n = 21), and 1.25 mg/kg (n=20). This study showed that for children aged 8–11 years, a 1.2 mg/kg dose would likely result in exposures comparable to those observed in adults resulting with the approved dosing regimen [see Dosage and Administration (2.3)].

Gender

In a pooled analysis of 38 women and 298 men participating in clinical pharmacology studies, there was no significant difference in the mean (±SD) tigecycline clearance between women (20.7±6.5 L/h) and men (22.8±8.7 L/h). Therefore, no dosage adjustment is necessary based on gender.

Race

In a pooled analysis of 73 Asian subjects, 53 Black subjects, 15 Hispanic subjects, 190 White subjects, and 3 subjects classified as "other" participating in clinical pharmacology studies, there was no significant difference in the mean (±SD) tigecycline clearance among the Asian subjects (28.8±8.8 L/h), Black subjects (23.0±7.8 L/h), Hispanic subjects (24.3±6.5 L/h), White subjects (22.1±8.9 L/h), and "other" subjects (25.0±4.8 L/h). Therefore, no dosage adjustment is necessary based on race.

Drug Interaction Studies

Digoxin

TYGACIL (100 mg followed by 50 mg every 12 hours) and digoxin (0.5 mg followed by 0.25 mg, orally, every 24 hours) were co-administered to healthy subjects in a drug interaction study. Tigecycline slightly decreased the Cmax of digoxin by 13%, but did not affect the AUC or clearance of digoxin. This small change in Cmax did not affect the steady-state pharmacodynamic effects of digoxin as measured by changes in ECG intervals. In addition, digoxin did not affect the pharmacokinetic profile of tigecycline. Therefore, no dosage adjustment of either drug is necessary when TYGACIL is administered with digoxin.

Warfarin

Concomitant administration of TYGACIL (100 mg followed by 50 mg every 12 hours) and warfarin (25 mg single-dose) to healthy subjects resulted in a decrease in clearance of R-warfarin and S-warfarin by 40% and 23%, an increase in Cmax by 38% and 43% and an increase in AUC by 68% and 29%, respectively. Tigecycline did not significantly alter the effects of warfarin on INR. In addition, warfarin did not affect the pharmacokinetic profile of tigecycline. However, prothrombin time or other suitable anticoagulation test should be monitored if tigecycline is administered with warfarin.

In vitro studies in human liver microsomes indicate that tigecycline does not inhibit metabolism mediated by any of the following 6 cytochrome P450 (CYP) isoforms: 1A2, 2C8, 2C9, 2C19, 2D6, and 3A4. Therefore, TYGACIL is not expected to alter the metabolism of drugs metabolized by these enzymes. In addition, because tigecycline is not extensively metabolized, clearance of tigecycline is not expected to be affected by drugs that inhibit or induce the activity of these CYP450 isoforms.

In vitro studies using Caco-2 cells indicate that tigecycline does not inhibit digoxin flux, suggesting that tigecycline is not a P-glycoprotein (P-gp) inhibitor. This in vitro information is consistent with the lack of effect of tigecycline on digoxin clearance noted in the in vivo drug interaction study described above.

Tigecycline is a substrate of P-gp based on an in vitro study using a cell line overexpressing P-gp. The potential contribution of P-gp-mediated transport to the in vivo disposition of tigecycline is not known. Coadministration of P-gp inhibitors (e.g., ketoconazole or cyclosporine) or P-gp inducers (e.g., rifampicin) could affect the pharmacokinetics of tigecycline.

12.4 Microbiology

Mechanism of Action

Tigecycline inhibits protein translation in bacteria by binding to the 30S ribosomal subunit and blocking entry of amino-acyl tRNA molecules into the A site of the ribosome. This prevents incorporation of amino acid residues into elongating peptide chains. In general, tigecycline is considered bacteriostatic; however, TYGACIL has demonstrated bactericidal activity against isolates of S. pneumoniae and L. pneumophila.

Resistance

To date there has been no cross-resistance observed between tigecycline and other antibacterial drugs. Tigecycline is less affected by the two major tetracycline-resistance mechanisms, ribosomal protection and efflux. Additionally, tigecycline is not affected by resistance mechanisms such as beta-lactamases (including extended spectrum beta-lactamases), target-site modifications, macrolide efflux pumps or enzyme target changes (e.g., gyrase/topoisomerases). However, some ESBL-producing isolates may confer resistance to tigecycline via other resistance mechanisms. Tigecycline resistance in some bacteria (e.g., Acinetobacter calcoaceticus-Acinetobacter baumannii complex) is associated with multi-drug resistant (MDR) efflux pumps.

Interaction with Other Antimicrobials

In vitro studies have not demonstrated antagonism between tigecycline and other commonly used antibacterial drugs.

Antimicrobial Activity

Tigecycline has been shown to be active against most isolates of the following microorganisms, both in vitro and in clinical infections [see Indications and Usage (1)].

Gram-positive bacteria

Enterococcus faecalis (vancomycin-susceptible isolates)
Staphylococcus aureus (methicillin-susceptible and -resistant isolates)
Streptococcus agalactiae
Streptococcus anginosus group (includes S. anginosus, S. intermedius, and S. constellatus)
Streptococcus pneumoniae (penicillin-susceptible isolates)
Streptococcus pyogenes

Gram-negative bacteria

Citrobacter freundii
Enterobacter cloacae
Escherichia coli
Haemophilus influenzae
Klebsiella oxytoca
Klebsiella pneumoniae
Legionella pneumophila

Anaerobic bacteria

Bacteroides fragilis
Bacteroides thetaiotaomicron
Bacteroides uniformis
Bacteroides vulgatus
Clostridium perfringens
Peptostreptococcus micros

The following in vitro data are available, but their clinical significance is unknown. At least 90 percent of the following bacteria exhibit an in vitro minimum inhibitory concentration (MIC) less than or equal to the susceptible breakpoint for tigecycline against isolates of similar genus or organism group. However, the efficacy of tigecycline in treating clinical infections caused by these bacteria has not been established in adequate and well-controlled clinical trials.

Gram-positive bacteria

Enterococcus avium
Enterococcus casseliflavus
Enterococcus faecalis (vancomycin-resistant isolates)
Enterococcus faecium (vancomycin-susceptible and -resistant isolates)
Enterococcus gallinarum
Listeria monocytogenes
Staphylococcus epidermidis (methicillin-susceptible and -resistant isolates)
Staphylococcus haemolyticus

Gram-negative bacteria

Acinetobacter baumannii [There have been reports of the development of tigecycline resistance in Acinetobacter infections seen during the course of standard treatment. Such resistance appears to be attributable to an MDR efflux pump mechanism. While monitoring for relapse of infection is important for all infected patients, more frequent monitoring in this case is suggested. If relapse is suspected, blood and other specimens should be obtained and cultured for the presence of bacteria. All bacterial isolates should be identified and tested for susceptibility to tigecycline and other appropriate antimicrobials.]
Aeromonas hydrophila
Citrobacter koseri
Enterobacter aerogenes
Haemophilus influenzae (ampicillin-resistant)
Haemophilus parainfluenzae
Pasteurella multocida
Serratia marcescens
Stenotrophomonas maltophilia

Anaerobic bacteria

Bacteroides distasonis
Bacteroides ovatus
Peptostreptococcus spp.
Porphyromonas spp.
Prevotella spp.

Other bacteria

Mycobacterium abscessus
Mycobacterium fortuitum

Susceptibility Testing

For specific information regarding susceptibility test interpretive criteria, and associated test methods and quality control standards recognized by FDA for this drug, please see https://www.fda.gov/STIC.

13 NONCLINICAL TOXICOLOGY

13.1 Carcinogenesis, Mutagenesis, Impairment of Fertility

Lifetime studies in animals have not been performed to evaluate the carcinogenic potential of tigecycline. No mutagenic or clastogenic potential was found in a battery of tests, including in vitro chromosome aberration assay in Chinese hamster ovary (CHO) cells, in vitro forward mutation assay in CHO cells (HGRPT locus), in vitro forward mutation assays in mouse lymphoma cells, and in vivo mouse micronucleus assay. Tigecycline did not affect mating or fertility in rats at exposures up to 5 times the human daily dose based on AUC (28 mcg∙hr/mL at 12 mg/kg/day). In female rats, there were no compound-related effects on ovaries or estrous cycles at exposures up to 5 times the human daily dose based on AUC.

13.2 Animal Toxicology and/or Pharmacology

In two week studies, decreased erythrocytes, reticulocytes, leukocytes, and platelets, in association with bone marrow hypocellularity, have been seen with tigecycline at exposures of 8 times and 10 times the human daily dose based on AUC in rats and dogs, (AUC of approximately 50 and 60 mcg∙hr/mL at doses of 30 and 12 mg/kg/day) respectively. These alterations were shown to be reversible after two weeks of dosing.

14 CLINICAL STUDIES

14.1 Complicated Skin and Skin Structure Infections

TYGACIL was evaluated in adults for the treatment of complicated skin and skin structure infections (cSSSI) in two randomized, double-blind, active-controlled, multinational, multicenter studies (Studies 1 and 2). These studies compared TYGACIL (100 mg intravenous initial dose followed by 50 mg every 12 hours) with vancomycin (1 g intravenous every 12 hours)/aztreonam (2 g intravenous every 12 hours) for 5 to 14 days. Patients with complicated deep soft tissue infections including wound infections and cellulitis (≥10 cm, requiring surgery/drainage or with complicated underlying disease), major abscesses, infected ulcers, and burns were enrolled in the studies. The primary efficacy endpoint was the clinical response at the test of cure (TOC) visit in the co-primary populations of the clinically evaluable (CE) and clinical modified intent-to-treat (c-mITT) patients. See Table 4. Clinical cure rates at TOC by pathogen in the microbiologically evaluable patients are presented in Table 5.

Table 4. Clinical Cure Rates from Two Studies in Complicated Skin and Skin Structure Infections after 5 to 14 Days of Therapy
 | TYGACIL [100 mg initially, followed by 50 mg every 12 hours] n/N (%) | Vancomycin/Aztreonam [Vancomycin (1 g every 12 hours)/Aztreonam (2 g every 12 hours)] n/N (%)
Study 1
CE | 165/199 (82.9) | 163/198 (82.3)
c-mITT | 209/277 (75.5) | 200/260 (76.9)
Study 2
CE | 200/223 (89.7) | 201/213 (94.4)
c-mITT | 220/261 (84.3) | 225/259 (86.9)

Table 5. Clinical Cure Rates By Infecting Pathogen in Microbiologically Evaluable Patients with Complicated Skin and Skin Structure Infections [Two cSSSI pivotal studies and two Resistant Pathogen studies]
Pathogen | TYGACIL n/N (%) | Vancomycin/Aztreonam n/N (%)
Escherichia coli | 29/36 (80.6) | 26/30 (86.7)
Enterobacter cloacae | 10/12 (83.3) | 15/15 (100)
Enterococcus faecalis (vancomycin-susceptible only) | 15/21 (71.4) | 19/24 (79.2)
Klebsiella pneumoniae | 12/14 (85.7) | 15/16 (93.8)
Methicillin-susceptible Staphylococcus aureus (MSSA) | 124/137 (90.5) | 113/120 (94.2)
Methicillin-resistant Staphylococcus aureus (MRSA) | 79/95 (83.2) | 46/57 (80.7)
Streptococcus agalactiae | 8/8 (100) | 11/14 (78.6)
Streptococcus anginosus grp. [Includes Streptococcus anginosus, Streptococcus intermedius, and Streptococcus constellatus] | 17/21 (81.0) | 9/10 (90.0)
Streptococcus pyogenes | 31/32 (96.9) | 24/27 (88.9)
Bacteroides fragilis | 7/9 (77.8) | 4/5 (80.0)

14.2 Complicated Intra-abdominal Infections

TYGACIL was evaluated in adults for the treatment of complicated intra-abdominal infections (cIAI) in two randomized, double-blind, active-controlled, multinational, multicenter studies (Studies 1 and 2). These studies compared TYGACIL (100 mg intravenous initial dose followed by 50 mg every 12 hours) with imipenem/cilastatin (500 mg intravenous every 6 hours) for 5 to 14 days. Patients with complicated diagnoses including appendicitis, cholecystitis, diverticulitis, gastric/duodenal perforation, intra-abdominal abscess, perforation of intestine, and peritonitis were enrolled in the studies. The primary efficacy endpoint was the clinical response at the TOC visit for the co-primary populations of the microbiologically evaluable (ME) and the microbiologic modified intent-to-treat (m-mITT) patients. See Table 6. Clinical cure rates at TOC by pathogen in the microbiologically evaluable patients are presented in Table 7.

Table 6. Clinical Cure Rates from Two Studies in Complicated Intra-abdominal Infections after 5 to 14 Days of Therapy
 | TYGACIL [100 mg initially, followed by 50 mg every 12 hours] n/N (%) | Imipenem/Cilastatin [Imipenem/Cilastatin (500 mg every 6 hours)] n/N (%)
Study 1
ME | 199/247 (80.6) | 210/255 (82.4)
m-mITT | 227/309 (73.5) | 244/312 (78.2)
Study 2
ME | 242/265 (91.3) | 232/258 (89.9)
m-mITT | 279/322 (86.6) | 270/319 (84.6)

Table 7. Clinical Cure Rates By Infecting Pathogen in Microbiologically Evaluable Patients with Complicated Intra-abdominal Infections [Two cIAI pivotal studies and two Resistant Pathogen studies]
Pathogen | TYGACIL n/N (%) | Imipenem/Cilastatin n/N (%)
Citrobacter freundii | 12/16 (75.0) | 3/4 (75.0)
Enterobacter cloacae | 15/17 (88.2) | 16/17 (94.1)
Escherichia coli | 284/336 (84.5) | 297/342 (86.8)
Klebsiella oxytoca | 19/20 (95.0) | 17/19 (89.5)
Klebsiella pneumoniae | 42/47 (89.4) | 46/53 (86.8)
Enterococcus faecalis | 29/38 (76.3) | 35/47 (74.5)
Methicillin-susceptible Staphylococcus aureus (MSSA) | 26/28 (92.9) | 22/24 (91.7)
Methicillin-resistant Staphylococcus aureus (MRSA) | 16/18 (88.9) | 1/3 (33.3)
Streptococcus anginosus grp. [Includes Streptococcus anginosus, Streptococcus intermedius, and Streptococcus constellatus] | 101/119 (84.9) | 60/79 (75.9)
Bacteroides fragilis | 68/88 (77.3) | 59/73 (80.8)
Bacteroides thetaiotaomicron | 36/41 (87.8) | 31/36 (86.1)
Bacteroides uniformis | 12/17 (70.6) | 14/16 (87.5)
Bacteroides vulgatus | 14/16 (87.5) | 4/6 (66.7)
Clostridium perfringens | 18/19 (94.7) | 20/22 (90.9)
Peptostreptococcus micros | 13/17 (76.5) | 8/11 (72.7)

14.3 Community-Acquired Bacterial Pneumonia

TYGACIL was evaluated in adults for the treatment of community-acquired bacterial pneumonia (CABP) in two randomized, double-blind, active-controlled, multinational, multicenter studies (Studies 1 and 2). These studies compared TYGACIL (100 mg intravenous initial dose followed by 50 mg every 12 hours) with levofloxacin (500 mg intravenous every 12 or 24 hours). In Study 1, after at least 3 days of intravenous therapy, a switch to oral levofloxacin (500 mg daily) was permitted for both treatment arms. Total therapy was 7 to 14 days. Patients with community-acquired bacterial pneumonia who required hospitalization and intravenous therapy were enrolled in the studies. The primary efficacy endpoint was the clinical response at the test of cure (TOC) visit in the co-primary populations of the clinically evaluable (CE) and clinical modified intent-to-treat (c-mITT) patients. See Table 8. Clinical cure rates at TOC by pathogen in the microbiologically evaluable patients are presented in Table 9.

Table 8. Clinical Cure Rates from Two Studies in Community-Acquired Bacterial Pneumonia after 7 to 14 Days of Total Therapy
 | TYGACIL [100 mg initially, followed by 50 mg every 12 hours] n/N (%) | Levofloxacin [Levofloxacin (500 mg intravenous every 12 or 24 hours)] n/N (%) | 95% CI [95% confidence interval for the treatment difference]
Study 1 [After at least 3 days of intravenous therapy, a switch to oral levofloxacin (500 mg daily) was permitted for both treatment arms in Study 1.]
CE | 125/138 (90.6) | 136/156 (87.2) | (-4.4, 11.2)
c-mITT | 149/191 (78) | 158/203 (77.8) | (-8.5, 8.9)
Study 2
CE | 128/144 (88.9) | 116/136 (85.3) | (-5.0, 12.2)
c-mITT | 170/203 (83.7) | 163/200 (81.5) | (-5.6, 10.1)

Table 9. Clinical Cure Rates By Infecting Pathogen in Microbiologically Evaluable Patients with Community-Acquired Bacterial Pneumonia [Two CABP studies]
Pathogen | TYGACIL n/N (%) | Levofloxacin n/N (%)
Haemophilus influenzae | 14/17 (82.4) | 13/16 (81.3)
Legionella pneumophila | 10/10 (100.0) | 6/6 (100.0)
Streptococcus pneumoniae (penicillin-susceptible only) [Includes cases of concurrent bacteremia [cure rates of 20/22 (90.9%) versus 13/18 (72.2%) for TYGACIL and levofloxacin respectively]] | 44/46 (95.7) | 39/44 (88.6)

To further evaluate the treatment effect of tigecycline, a post-hoc analysis was conducted in CABP patients with a higher risk of mortality, for whom the treatment effect of antibacterial drugs is supported by historical evidence. The higher-risk group included CABP patients from the two studies with any of the following factors:

- Age ≥50 years
- PSI score ≥3
- Streptococcus pneumoniae bacteremia

The results of this analysis are shown in Table 10. Age ≥50 was the most common risk factor in the higher-risk group.

Table 10. Post-hoc Analysis of Clinical Cure Rates in Patients with Community-Acquired Bacterial Pneumonia Based on Risk of Mortality [Patients at higher risk of death include patients with any one of the following: ≥50 year of age; PSI score ≥3; or bacteremia due to Streptococcus pneumoniae]
 | TYGACIL n/N (%) | Levofloxacin n/N (%) | 95% CI [95% confidence interval for the treatment difference]
Study 1 [After at least 3 days of intravenous therapy, a switch to oral levofloxacin (500 mg daily) was permitted for both treatment arms in Study 1.]
CE
Higher risk
Yes | 93/103 (90.3) | 84/102 (82.4) | (-2.3, 18.2)
No | 32/35 (91.4) | 52/54 (96.3) | (-20.8, 7.1)
c-mITT
Higher risk
Yes | 111/142 (78.2) | 100/134 (74.6) | (-6.9, 14)
No | 38/49 (77.6) | 58/69 (84.1) | (-22.8, 8.7)
Study 2
CE
Higher risk
Yes | 95/107 (88.8) | 68/85 (80) | (-2.2, 20.3)
No | 33/37 (89.2) | 48/51 (94.1) | (-21.1, 8.6)
c-mITT
Higher risk
Yes | 112/134 (83.6) | 93/120 (77.5) | (-4.2, 16.4)
No | 58/69 (84.1) | 70/80 (87.5) | (-16.2, 8.8)

16 HOW SUPPLIED/STORAGE AND HANDLING

TYGACIL (tigecycline) for injection is supplied in a single-dose 10 mL glass vial, containing 50 mg tigecycline lyophilized powder for reconstitution.

Supplied:

Unit of Sale | Total Content
NDC 0008-4990-20 Box containing 10 single-dose vials | 50 mg/vial

STORAGE AND HANDLING

Prior to reconstitution, TYGACIL should be stored at 20° to 25°C (68° to 77°F); excursions permitted to 15° to 30°C (59° to 86°F). [See USP Controlled Room Temperature.] The reconstituted solution of TYGACIL may be stored at room temperature (not to exceed 25°C/77°F) for up to 24 hours (up to 6 hours in the vial and the remaining time in the intravenous bag) [see Dosage and Administration (2.5)].

17 PATIENT COUNSELING INFORMATION

Tooth Discoloration and Inhibition of Bone Growth

Advise pregnant women that TYGACIL may cause permanent discoloration of deciduous teeth and reversible inhibition of bone growth when administered during the second and third trimesters of pregnancy [see Warnings and Precautions (5.7, 5.8) and Use in Specific Populations (8.1, 8.4)].

Lactation

Advise a woman not to breastfeed for longer than 3 weeks while taking TYGACIL because of the lack of data on effects due to prolonged breastfeeding, and the theoretical risk of dental discoloration and inhibition of bone growth. Women may also consider reducing infant exposure through pumping and discarding breastmilk during and for 9 days after the last dose of tigecycline [see Use in Specific Populations (8.2)].

Diarrhea

Advise patients, their families, or caregivers that diarrhea is a common problem caused by antibacterial drugs, including TYGACIL. Sometimes, frequent watery or bloody diarrhea may occur and may be a sign of a more serious intestinal infection. If severe watery or bloody diarrhea develops, advise patients to contact his or her healthcare provider [see Warnings and Precautions (5.9)].

Development of Resistance

Patients should be counseled that antibacterial drugs including TYGACIL should only be used to treat bacterial infections. They do not treat viral infections (e.g., the common cold). When TYGACIL is prescribed to treat a bacterial infection, patients should be told that although it is common to feel better early in the course of therapy, the medication should be taken exactly as directed. Skipping doses or not completing the full course of therapy may (1) decrease the effectiveness of the immediate treatment and (2) increase the likelihood that bacteria will develop resistance and will not be treatable by TYGACIL or other antibacterial drugs in the future.

This product's labeling may have been updated. For the most recent prescribing information, please visit www.pfizer.com.

LAB-0458-16.0

PRINCIPAL DISPLAY PANEL - 50 mg Vial Label

NDC 0008-4990-19

Single-dose Vial

Tygacil®
(tigecycline)
for injection

50 mg

tigecycline per vial
For I.V. Infusion Only

PRINCIPAL DISPLAY PANEL - 50 mg Vial Carton

10 Single-dose Vials

NDC 0008-4990-20
Contains 10 of NDC 0008-4990-19

Rx only

Tygacil®
(tigecycline)
for injection

50 mg

tigecycline per vial

Pfizer Hospital

RECONSTITUTED SOLUTION
MUST BE FURTHER DILUTED
FOR I.V. INFUSION